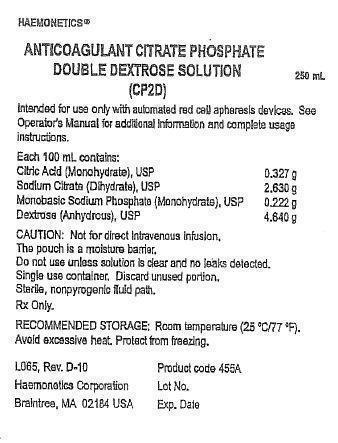 DRUG LABEL: Haemonetics Anticoagulant Citrate Phosphate Double Dextrose Solution (CP2D)
NDC: 57826-455 | Form: SOLUTION
Manufacturer: Haemonetics Corporation
Category: prescription | Type: HUMAN PRESCRIPTION DRUG LABEL
Date: 20200930

ACTIVE INGREDIENTS: CITRIC ACID MONOHYDRATE 32.7 mg/1 mL; TRISODIUM CITRATE DIHYDRATE 263 mg/1 mL; SODIUM PHOSPHATE, MONOBASIC, MONOHYDRATE 22.2 mg/1 mL; ANHYDROUS DEXTROSE 464 mg/1 mL
INACTIVE INGREDIENTS: WATER

Haemonetics Anticoagulant Citrate Phosphate Double Dextrose Solution (CP2D)

Instructions for Use

For use with Haemonetics Apheresis Devices
Rx Only

Products: Anticoagulant Citrate Phosphate Double Dextrose (CP2D)
and Additive Solution Formula 3 (AS-3)

Company:
Haemonetics Corporation
400 Wood Road
Braintree, MA 02184

I. Indications for Use

The Haemonetics 250mL Anticoagulant Citrate Phosphate Double Dextrose (CP2D)
and 250mL Additive Solution Formula 3 (AS-3) nutrient solution are intended to be
used only with automated apheresis devices for collecting human blood and blood
components. The anticoagulant solution is metered by the apheresis machine into
the collected whole blood. It is not to be infused directly into the donor. After the
anticoagulant is used, the bag in which it was contained is discarded. When
collecting plasma in the RBCP protocol, the plasma is collected into an empty plasma
collection bag. One hundred milliliters (100ml) of AS-3 is transferred into one RBC
collection bag when using the RBCP protocol or 2 separate bags when using the
2RBC protocol. AS-3 solution provides nutrients to keep the red blood cells viable for
42 days when refrigerated.

CP2D is also indicated for the collection of FFP and PF24 plasma, collected and
stored plasma collected using the 822, 822-2P and 822F-2P disposable sets may be
frozen within 8 hours (FFP) or within 24 hours which includes 8 hours room
temperature storage and 16 hours refrigeration storage (PF24).

The 300mL AS-3 is used in conjunction with automated red blood cell washing
devices. AS-3 serves as the nutrient solution for storage of the red blood cell product
after deglycerolization. The red blood cells are washed using the Model 215 System.
AS-3 is used for priming the disposable and for the last wash of the red blood cells.
The washed cells are then re-suspended in 100mL of the AS-3 before transfer into a
product collection bag or storage bag. Additive Solution Formula 3 (AS-3) provides
nutrients to keep the washed red blood cells viable for up to 14 days after washing
when refrigerated.

Neither the CP2D nor the AS-3 container is used for the storage of blood or blood
components.

Dosage Form

The container for all CP2D and AS-3 solutions is a flexible polyvinyl chloride (PVC)
bag sized for holding the appropriate amount of solution. The bag has a single port
that is used for bag filling. The port is sealed after filling with a male luer assembly
(CP2D) or female luer assembly (AS-3). Both the male and female luers are gamma
irradiated prior to use. The plastic bag is contained in an overwrap which is added
prior to sterilization.

The formulations for these products are as follows:

Citrate Phosphate Double Dextrose Solution (CP2D)
Each 100 mL contains:
Citric Acid (Monohydrate), USP 0.327 g
Sodium Citrate (Dihydrate), USP 2.630 g
Monobasic Sodium Phosphate (Monohydrate), USP 0.222 g
Dextrose (Anhydrous), USP 4.640 g

Additive Solution 3 (AS-3)
Each 100mL contains:
Citric Acid (Monohydrate), USP 0.042 g
Monobasic Sodium Phosphate (Monohydrate), USP 0.276 g
Sodium Chloride, USP 0.410 g
Adenine, USP 0.030 g
Dextrose (Anhydrous), USP 1.000 g
Sodium Citrate (Dihydrate), USP 0.588 g
containing 15 mEq of Sodium.

Dosage and Administration:

CP2D Anticoagulant Solution and AS-3 Solution may be used with Haemonetics
apheresis devices. See the Haemonetics Operation Manual for full operating
instructions.

Prior to use of the solutions, check the solutions for leaks by squeezing each of the
bags firmly. If leaks are found, discard the solution.

III. Clinical Data

Studies of the effectiveness of 250mL CP2D and 250mL AS-3 made by Haemonetics
Corporation Union, South Carolina facility included in vivo survival data in healthy
subjects at one test site and in vitro characterization of stored red blood cells at
three test sites.

Haemonetics Clinical Evaluation #95012, involved autologous in vivo recovery and
survival studies, and in vitro red blood cell characterization conducted at a single
site. RBC results collected with Haemonetics CP2D/AS-3 were compared to crossover
controls of manually collected RBCs from the same donors using CP2D/AS-3 made by
Medsep Corporation (crossover manual controls). In addition, results were
compared to data from other RBC apheresis donors using CP2D/AS-3 solutions
manufactured by MedSep (unmatched apheresis controls). Test parameters included
hematocrit, hemoglobin, RBC and WBC counts, ATP levels, pH, supernatant
potassium, free hemoglobin, supernatant glucose levels, and product weight. The
RBC quality of test units after 42-day storage was equivalent or slightly superior to
those of the control units. RBCs collected by the two different collection protocols
(Red Blood Cells with or without Plasma) showed no significant differences in terms
of RBC quality and red blood cells from all groups met FDA and AABB guidelines for
24-hour recovering at 42 days storage.

Study #98001 was performed using 250mL CP2D and 250mL AS-3 to confirm, in
vitro, the results of Clinical Evaluation #95012. Three test sites each performed three
RBCP and three 2RBC apheresis procedures using the MCS+ LN8150 and associated
collection sets. In addition, each site collected six manual whole blood units as
concurrent (unmatched) controls using Medsep sets and prepared RBCs according to
standard procedures.

In vitro tests of red blood cell functional and physical integrity were conducted at
Days 0 and 42 of storage. All plasma units from the RBCP and manual procedures
were evaluated on Day 0 for in vitro product characteristics. Group t-tests (two
tailed) were performed to examine any statistically significant differences between
the properties of apheresis and manual RBCs. Statistically significant differences
(p<n; 0.05) were evaluated in terms of clinical significance. Differences in glucose or
lactate levels, hematocrit, pH, and supernatant potassium were not considered
clinically relevant because these parameters have not been found to correlate
significantly with the in vivo 24 hour percent recovery.

The results from this study confirmed the observations from Clinical Evaluation
#95012. The quality of stored RBC products collected by apheresis is similar to RBC
products collected manually. A difference in ATP and hemolysis levels, both after
processing and on day 42 of storage, for the apheresis units were not statistically
significant when compared to ATP and hemolysis levels from manually collected
RBCs and were similar to historicai reference values.

AS-3 300ml was used in conjunction with an automated closed system, the
Haemonetics Model 215 (now called the ACP) in Clinical Evaluation #97002. Five test
sites were used in this study. 100 samples were tested in vitro and 30 in vivo. Red
blood cells derived from CPDA-1 whole blood units were used. AS-1 red blood cells
were used as a control. A total of 140 red blood cell units were glycerolized and
deglycerolized. The in vitro RBC quality and in vivo RBC viability data obtained on
these units demonstrate that red cell units glycerolized and deglycerolized using the
Model 215 System and resuspended in 300ml AS-3 solution manufactured by
Haemonetics, Union, South Carolina are processed in a closed system and can be
stored for 15 days at 4°C.

Clinical report TR-CLN-100229-A was conducted to support the use of CP2D for the
collection of FFP and PF24 {plasma collected and stored Plasma collected using the
822, 822-2P and 822F-2P disposable sets may be frozen within 8 hours (FFP) or
within 24 hours which includes 8 hours room temperature storage and 16 hours
refrigeration storage (PF24). The following tables provide a summary of the results
of this evaluation.

Note: Table 1, Table 2, and Table 3 below demonstrate the results of a clinical
study conducted for various coagulation factors on plasma that was frozen within
8 hours (FPP) versus plasma frozen within 24 hours, which includes 8 hours
room temperature storage and 16 hours refrigeration storage (PF24).

As noted in Table 1 below, Significant differences were observed between PF24 and
FFP for assays Prothrombine Time, Partial Thromboplastin Time, FVlla, and
FVIII.
Table 2 provides the results for Plasma Sample A, which was an outlier and
subsequently excluded from the analysis.

Table 3 provides a summary of how many samples tested in each group differed by
>20% when FFP and PF24 were compared.

Table 1, Summary of FFP and PFZ4 plasma product assays (N=59)
Assay | Mean (SD) |  | Median |  | (Min, Max) |  | Mean difference; (PF24, FFP) (95%; confidence; interval)
 | FFP | PF24 | FFP | PF24 | FFP | PF24
Prothrombin Time; (sec) | 12.0; (0.50) | 12.1; (0.59) | 11.9 | 12.1 | (11.2, 13.8) | (10.5, 14.0) | 015; (0.09,0.20)
Activated Partial Thromboplastin Time (sec) | 29.4; (3.32) | 30.3 (3.34) | 28.8 | 29.8 | (23.1, 38.5) | (24.1, 39.5) | 0.86; (0.64, 1.08)
Favtor V (%) | 120.1; (23.93) | 120.0; (23.88) | 120.0 | 120.0 | (61.0, 181.0) | (59.0, 182.0) | -0.14; (-2.03, 1.76)
Factor Vlla (mU/mL)* | 60.5; (26.95) | 45.0; (24.72) | 54.0 | 41.5 | (21.0, 131.0) | (12.0, 159.0) | -15 .50; (-19 .23, -11.77)
Factor VIII:C (%)* | 94.3; (34.24) | 81.7; (27.31) | 88.5 | 82.5 | (33.0, 194.0) | (34.0, 152.0) | -12.67; (-15.97, -9.38)
AT-III (%) | 97.8; (12.24) | 94.7; (15.97) | 98.0 | 95.0 | (71.0, 126.0) | (19.0, 134.0) | -3.05; (-6.30, 0.20)
Factor XI (%) | 112.2; (17.42) | 112.8; (18.46) | 113.0 | 113.0 | (81.0,151.0) | (82.0, 155.0) | 0.63; (-0.70,1.95)
vWF (R:Co) (% function) | 89.5; (35.65) | 89.4; (35.58) | 85.0 | 87.0 | (35.0, 179.0) | (37.0, 185.0) | -0.15; (-2.21, 1.91)
Protein S; (% activity) | 74.9; (19.61) | 73.4; (20.76) | 72.0 | 71.0 | (33.0, 125.0) | (39.0, 126.0) | -1.49; (-3.81, 0.83)
Protein C (% activity) | 117.1; (17.59) | 117.7; (17.49) | 115.0 | 118.0 | (65.0,157.0) | (68.0, 162.0) | 0.53; (-0.54,1.59)
Fibrinopeptide F 1.2; (pmol/L)* | 136.4; (63.34) | 133.1; (55.15) | 113.0 | 114.0 | (80.0, 344.0) | (80.0,331.0) | -3.29; (-8.37,1.78)
Thrombln-Anti-; thrombin Complex; (ng/mL) | 2.3; (1.38) | 2.1; (0.40) | 2.0 | 2.0 | (2.0, 12.4) | (2.0,4.8) | -0.17; (-0 .53, 0.18)

*Sample size = 58. The outlier pair was excluded from the analysis based on the statistical criteria or laboratory errors.

One sample (Plasma Sample A) showed significantly increased levels for Factor VIIa and F1.2. Another sample (Plasma Sample B) showed significantly decreased level of Factor VIII:C for the FFP sample (Table 2). These data were excluded from Table 1 since the values for VIIa and F1.2 were more than 4 SD from the mean. The factor VIII:C was not more than 4 SD from the mean but was significantly lower in FFP as compared to PF24. While other parameters in this sample did not show significant differences when compared to the control FFP, the FDA could not exclude the possibility that the activation found in the PF24 sample was related to the preparation procedure. The rate of such event occurrence was unknown and, based on review of published values for PF24 products, is most likely very rare. The clinical significance of the elevated markers of clotting activation for transfusion recipients is undetermined.

Table 2, Three outlier pairs in plasma measurements
Subject # | Measurement | FFP | PF24 | Range | without | the | outliers
 |  |  |  | FFP Min | FFP; Max | PF24; Min | PF24; Max
RBCP16 | Factor FVIIa (mU/mL) | 220 | 767 | 21 | 131 | 12 | 159
RBCP16 | F1.2 (pmol/L) | 702 | 1940 | 80 | 344 | 80 | 331
RBCP01 | Factor VIII: C(%) | 2 | 63 | 33 | 194 | 34 | 152

Table 3, Proportion of Paired Sample:PF24 is greater than or less than FFP by more than 20%
Assay | PFZ4>FFP by more than 20% | PF24<FFP by more than 20%
Prothrombine Time (sec) | 0% (0/59) | 0% (0/59)
Partial Thromboplastin Time (sed | 0% (0/59) | 0% (0/59)
Factor V (%) | 1.7% (1/59) | 0% (0/59)
Factor Vila (mU/mL) | 3.4% (2/58) | 89.7% (52/58)
AT-III (%) | 1.7% (1/59) | 8.5% (5/59)
Factor VIII :C (%) | 1.7% (1/58) | 22.4% (13/58)
Factor XI (%) | 0% (0/59) | 0% (0/59)
Fibrinopeptide 1.2 (pmol/L) | 0%(0/58) | 1.7% (1/58)
Protein C (% activity) | 0% (0/59) | 0% (0/59)
Protein S (% activity) | 5.1% (3/59) | 1.7% (1/59)
Thrombin-Antithrombin Complex; (ng/mL) | 1.7% (1/59) | 3.4% (2/59)
vWF (% activity) | 3.4% (2/59) | 1.7% (1/59)

Note: Plasma collected may be labeled as FFP or Plasma Frozen within 24 Hours (PF24).

Note: For FFP, the plasma should be placed in a freezer within 8 hours from the completion of collection. The plasma should be frozen at -18°C or colder.
For product intended to be labeled as PF24, the plasma should be refrigerated within 8 hours of collection at 1 – 6°C and frozen within 24 hours of collection.
FFP and PF24 should be frozen at -18°C or colder.

IV. Warnings and Cautions

Contraindications:
None known

Precautions for use:
• Solutions are NOT INTENDED FOR DIRECT INFUSION.
• Do not use if particulate matter is present or if the solution is cloudy
Note: Some opacity of the plastic container due to moisture absorbance by
the PVC during the sterilization process may be observed. This is normal and
does not affect the quality or the safety of the product. This white, hazy
appearance will diminish gradually over time. This advice only applies to the
plastic container. Do not use if the solution itself is cloudy or contains
particulate matter.
•Do not use if the container is damaged, leaking or if there is any visible sign
of deterioration.
Note: The over wrap serves as a moisture barrier. Upon removing the
solution bag, small droplets of condensation may be present in the
packaging. This is considered normal. After removing the over wrap gently
squeeze the inner bag which protects the sterility of the solution. Discard if
any leaks are observed or if an excessive amount of solution is noted within
the over wrap.
• Do not reuse solution. Discard any unused or partially used solutions.
• Protect from sharp objects.
• Verify that solutions have been appropriately connected to avoid leaks.
• The set should be loaded and primed for use within 8 hours of the start of the collection.
• Carry out the apheresis procedure in accordance with the detailed
instructions of the manufacturer of the apheresis device.

Adverse Reactions:

Donors being reinfused with citrated blood or blood components may experience
side effects due to the presence of citrate. Patients being transfused with the blood
components could also experience a reaction to the citrated blood components.
The major symptom experienced by donors is paraesthesia. Should this occur the
reinfusion should be stopped or the reinfusion rate decreased. In the event of
inadvertent bolus of the product administer calcium gluconate.

Drug Abuse / Dependence:

Both solutions are intended to be used only with automated apheresis devices for
collecting human blood and blood components. CP2D is used as an anticoagulant
solution and AS-3 is intended for use a nutrient solution. Neither solution is
intended for direct infusion; neither solution produces a pharmacological effect.

Overdosage:

Both solutions are intended to be used only with automated apheresis devices for
collecting human blood and blood components. CP2D is used as an anticoagulant
solution and AS-3 is intended for use a nutrient solution. Neither solution is
intended for direct infusion.

How Supplied:

250mL CP2D Anticoagulant Solution is supplied in flexible PVC containers with a
sterile, non-pyrogenic fluid path.
250mL and 300mL AS-3 Nutrient Solution is supplied in flexible PVC containers with
a sterile, non-pyrogenic fluid path.

Storage and Handling:

Room temperature (25°C/77°F). Avoid excessive heat. Protect from freezing.

113692-00(AB)

Package Label

HAEMONETICS®
ANTICOAGULANT CITRATE PHOSPHATE
DOUBLE DEXTROSE SOLUTION
(CP2D)

Intended for use only with automated red cell apheresis devices to collect
red blood cells and plasma (FFP and PF24). See the appropriate Operator’s
manual for additional information and complete usage instructions.

Each 100 mL contains:
Citric Acid (Monohydrate), USP 0.327 g
Sodium Citrate (Dihydrate), USP 2.630 g
Monobasic Sodium Phosphate (Monohydrate), USP 0.222 g
Dextrose (Anhydrous), USP 4.640 g

CAUTION: Not for direct intravenous infusion.
The pouch is a moisture barrier.
Do not use unless solution is clear and no leaks detected.
Single use container. Discard unused portion.
Sterile, nonpyrogenic fluid path.
Rx Only

RECOMENDED STORAGE: Room Temperature (25°C / 77°F)
Avoid excessive heat. Protect from freezing.

L065 DA Product code 455A
Haemonetics Corporation Lot No.
Braintree, MA 02184 USA Exp Date